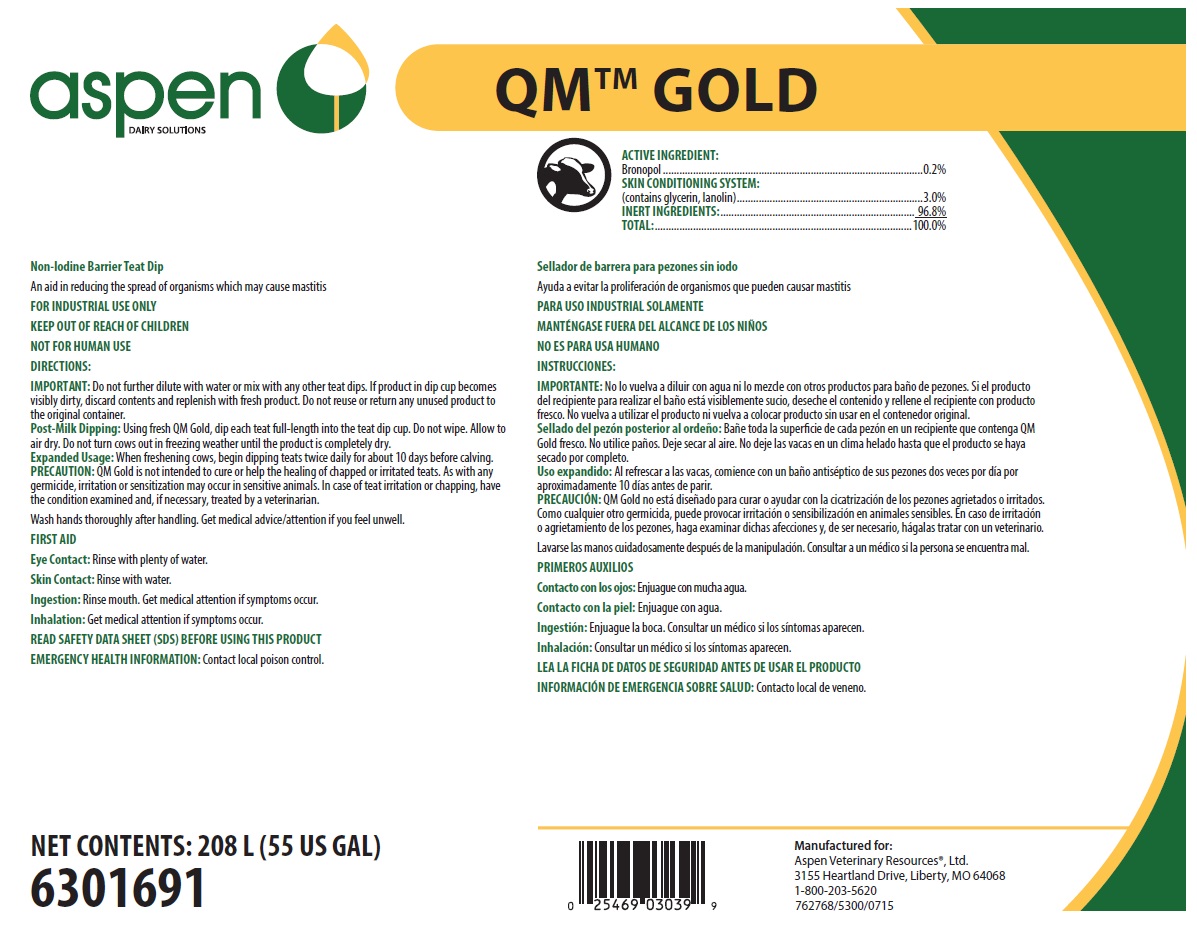 DRUG LABEL: QM Gold
NDC: 46066-409 | Form: SOLUTION
Manufacturer: Animal Health International, Inc.
Category: animal | Type: OTC ANIMAL DRUG LABEL
Date: 20230306

ACTIVE INGREDIENTS: BRONOPOL 2 mg/1 mL
INACTIVE INGREDIENTS: WATER; GLYCERIN; PEG-75 LANOLIN

SAFE HANDLING WARNING

FOR INDUSTRIAL USE ONLY

KEEP OUT OF REACH OF CHILDREN

NOT FOR HUMAN USE

Wash hands thoroughly after handling. Get medical advice/attention if you feel unwell.

DIRECTIONS:

IMPORTANT: Do not further dilute with water or mix with any other teat dips. If product in dip cup becomes visibly dirty, discard contents and replenish with fresh product. Do not reuse or return any unused product to the original container.

Post-Milk Dipping: Using fresh QM Gold, dip each teat full-length into the teat dip cup. Do not wipe. Allow to air dry. Do not turn cows out in freezing weather until the product is completely dry.

Expanded Usage: When freshening cows, begin dipping teats twice daily for about 10 days before calving. PRECAUTION: QM Gold is not intended to cure or help the healing of chapped or irritated teats. As with any germicide, irritation or sensitization may occur in sensitive animals. In case of teat irritation or chapping, have the condition examined and, if necessary, treated by a veterinarian.

PRECAUTION: QM Gold is not intended to cure or help the healing of chapped or irritated teats. As with any germicide, irritation or sensitization may occur in sensitive animals. In case of teat irritation or chapping, have the condition examined and, if necessary, treated by a veterinarian.

OTHER SAFETY INFORMATION

FIRST AID

Eye Contact: Rinse with plenty of water.

Skin Contact: Rinse with water.

Ingestion: Rinse mouth. Get medical attention if symptoms occur.

Inhalation: Get medical attention if symptoms occur.

READ SAFETY DATA SHEET (SDS) BEFORE USING THIS PRODUCT

EMERGENCY HEALTH INFORMATION: Contact local poison control.

PACKAGE LABEL

pen DAIRY SOLUTIONS

QM™ GOLD

Non-Iodine Barrier Teat Dip
An aid in reducing the spread of organisms which may cause mastitis

ACTIVE INGREDIENT:

Bronopol............................0.2%

SKIN CONDITIONING SYSTEM:

(contains glycerin, lanolin)...3.0%

INERT INGREDIENTS:........96.8%

TOTAL:...........................100.0%

NET CONTENTS: 208 L (55 US GAL)
6301691

Manufactured for:
Aspen Veterinary Resources®, Ltd. 3155 Heartland Drive, Liberty, MO 64068
1-800-203-5620
762768/5300/0715